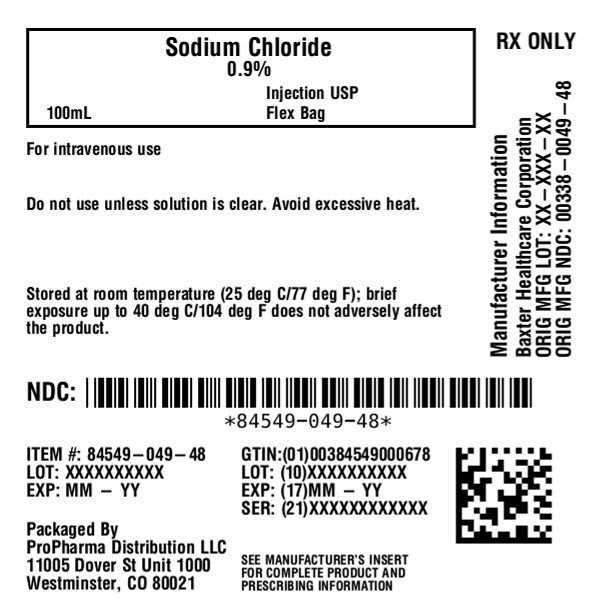 DRUG LABEL: Sodium Chloride
NDC: 84549-049 | Form: INJECTION, SOLUTION
Manufacturer: ProPharma Distribution
Category: prescription | Type: HUMAN PRESCRIPTION DRUG LABEL
Date: 20251218

ACTIVE INGREDIENTS: SODIUM CHLORIDE 9 g/1000 mL
INACTIVE INGREDIENTS: WATER

Sodium Chloride Injection, USP
in VIAFLEX Plastic Container

DESCRIPTION

Sodium Chloride Injection, USP is a sterile, nonpyrogenic solution for fluid and electrolyte replenishment in single dose containers for intravenous administration. It contains no antimicrobial agents. The nominal pH is 5.0 (4.5 to 7.0). Composition, osmolarity, and ionic concentration are shown below:

0.45% Sodium Chloride Injection, USPcontains 4.5 g/L Sodium Chloride, USP (NaCl) and is hypotonic with an osmolarity of 154 mOsmol/L (calc). It contains 77 mEq/L sodium and 77 mEq/L chloride.

0.9% Sodium Chloride Injection, USPcontains 9 g/L Sodium Chloride, USP (NaCl) with an osmolarity of 308 mOsmol/L (calc). It contains 154 mEq/L sodium and 154 mEq/L chloride.

The VIAFLEX plastic container is fabricated from a specially formulated polyvinyl chloride (PL 146 Plastic). The amount of water that can permeate from inside the container into the overwrap is insufficient to affect the solution significantly. Solutions in contact with the plastic container can leach out certain of its chemical components in very small amounts within the expiration period, e.g., di-2- ethylhexyl phthalate (DEHP), up to 5 parts per million. However, the safety of the plastic has been confirmed in tests in animals according to USP biological tests for plastic containers as well as by tissue culture toxicity studies.

CLINICAL PHARMACOLOGY

Sodium Chloride Injection, USP has value as a source of water and electrolytes. It is capable of inducing diuresis depending on the clinical condition of the patient.

INDICATIONS AND USAGE

Sodium Chloride Injection, USP is indicated as a source of water and electrolytes.

0.9% Sodium Chloride Injection, USP is also indicated for use as a priming solution in hemodialysis procedures.

CONTRAINDICATIONS

None known.

WARNINGS

Hypersensitivity

Hypersensitivity and infusion reactions, including hypotension, pyrexia, tremor, chills, urticaria, rash, and pruritus have been reported with 0.9% Sodium Chloride Injection, USP and may occur with 0.45% Sodium Chloride Injection, USP.

Stop the infusion immediately if signs or symptoms of a hypersensitivity reaction develop, such as tachycardia, chest pain, dyspnea and flushing. Appropriate therapeutic countermeasures must be instituted as clinically indicated.

Electrolyte Imbalances

Fluid Overload

Depending on the volume and rate of infusion, and the patient’s underlying clinical condition, the intravenous administration of Sodium Chloride Injection, USP can cause fluid disturbances such as overhydration/hypervolemia and congested states, including pulmonary congestion and edema.

Avoid 0.9% Sodium Chloride Injection, USP in patients with or at risk for fluid and/or solute overloading. If use cannot be avoided, monitor fluid balance, electrolyte concentrations, and acid base balance, as needed and especially during prolonged use.

Hyponatremia

Sodium Chloride Injection, USP may cause hyponatremia. Hyponatremia can lead to acute hyponatremic encephalopathy characterized by headache, nausea, seizures, lethargy, and vomiting. Patients with brain edema are at particular risk of severe, irreversible and life-threatening brain injury.

The risk of hospital-acquired hyponatremia is increased in patients with cardiac or pulmonary failure, and in patients with non-osmotic vasopressin release (including SIADH) treated with high volume of Sodium Chloride Injection, USP.

The risk for hyponatremia is increased in pediatric patients, elderly patients, postoperative patients, those with psychogenic polydipsia, and in patients treated with medications that increase the risk of hyponatremia (such as diuretics, certain antiepileptic and psychotropic medications). See DRUG INTERACTIONS.

Patients at increased risk for developing complications of hyponatremia such as hyponatremic encephalopathy, include pediatric patients, women (in particular pre-menopausal women), patients with hypoxemia, and patients with underlying central nervous system disease. Avoid Sodium Chloride Injection, USP in patients with or at risk for hyponatremia. If use cannot be avoided, monitor serum sodium concentrations.

Rapid correction of hyponatremia is potentially dangerous with risk of serious neurologic complications. Brain adaptations reducing risk of cerebral edema make the brain vulnerable to injury when chronic hyponatremia is too rapidly corrected, which is known as osmotic demyelination syndrome (ODS). To avoid complications, monitor serum sodium and chloride concentrations, fluid status, acid-base balance, and signs of neurologic complications.

Hypernatremia

Hypernatremia may occur with Sodium Chloride Injection, USP. Conditions that may increase the risk of hypernatremia, fluid overload and edema (central and peripheral), include patients with: primary hyperaldosteronism; secondary hyperaldosteronism

associated with, for example, hypertension, congestive heart failure, liver disease (including cirrhosis), renal disease (including renal artery stenosis, nephrosclerosis); and pre-eclampsia.

Certain medications, such as corticosteroids or corticotropin, may also increase risk of sodium and fluid retention, see DRUG INTERACTIONS.

Avoid Sodium Chloride Injection, USP in patients with, or at risk for, hypernatremia. If use cannot be avoided, monitor serum sodium concentrations.

Rapid correction of hypernatremia is potentially dangerous with risk of serious neurologic complications. Excessively rapid correction of hypernatremia is also associated with a risk for serious neurologic complications such as osmotic demyelination syndrome (ODS) with risk of seizures and cerebral edema.

PRECAUTIONS

Patients with Severe Renal Impairment

Administration of Sodium Chloride Injection, USP in patients with or at risk of severe renal impairment, may result in hypernatremia and/or fluid overload (see WARNINGS). Avoid Sodium Chloride Injection, USP in patients with severe renal impairment or conditions that may cause sodium and/or potassium retention, fluid overload, or edema. If use cannot be avoided, monitor patients with severe renal impairment for development of these adverse reactions.

Drug Interactions

Other Products that Affect Fluid and/or Electrolyte Balance

Administration of Sodium Chloride Injection, USP to patients treated concomitantly with drugs associated with sodium and fluid retention may increase the risk of hypernatremia and volume overload. Avoid use of Sodium Chloride Injection, USP in patients receiving such products, such as corticosteroids or corticotropin. If use cannot be avoided, monitor serum electrolytes, fluid balance and acid-base balance.

Lithium

Renal sodium and lithium clearance may be decreased during administration of 0.45% Sodium Chloride Injection, USP. Monitor serum lithium concentrations during concomitant use.

Renal sodium and lithium clearance may be increased during administration of 0.9% Sodium Chloride Injection, USP. Monitor serum lithium concentrations during concomitant use.

Other Drugs that Increase the Risk of Hyponatremia

Administration of Sodium Chloride Injection, USP in patients treated concomitantly with medications associated with hyponatremia may increase the risk of developing hyponatremia.

Avoid use of Sodium Chloride Injection, USP in patients receiving products, such as diuretics, and certain antiepileptic and psychotropic medications. Drugs that increase the vasopressin effect reduce renal electrolyte free water excretion and may also increase the risk of hyponatremia following treatment with intravenous fluids. If use cannot be avoided, monitor serum sodium concentrations.

Pregnancy

There are no adequate and well controlled studies with Sodium Chloride Injection, USP in pregnant women and animal reproduction studies have not been conducted with this drug. Therefore, it is not known whether Sodium Chloride Injection, USP can cause fetal harm when administered to a pregnant woman. Sodium Chloride Injection, USP should be given during pregnancy only if the potential benefit justifies the potential risk to the fetus.

Nursing Mothers

It is not known whether this drug is present in human milk. Because many drugs are present in human milk, caution should be exercised when Sodium Chloride Injection, USP is administered to a nursing woman.

Pediatric Use

The use of Sodium Chloride Injection, USP in pediatric patients is based on clinical practice. (See DOSAGE AND ADMINISTRATION).

Closely monitor plasma electrolyte concentrations in pediatric patients who may have impaired ability to regulate fluids and electrolytes. In very low birth weight infants, excessive or rapid administration of Sodium Chloride Injection, USP may result in increased serum osmolality and risk of intracerebral hemorrhage.

Children (including neonates and older children) are at increased risk of developing hyponatremia as well as for developing hyponatremic encephalopathy.

Geriatric Use

Geriatric patients are at increased risk of developing electrolyte imbalances. Sodium Chloride Injection, USP is known to be substantially excreted by the kidney, and the risk of toxic reactions to this drug may be greater in patients with impaired renal function. Therefore, dose selection for an elderly patient should be cautious, usually starting at the low end of the dosing range, reflecting the greater frequency of decreased hepatic, renal, or cardiac function, and of concomitant disease or other drug therapy. Consider monitoring renal function in elderly patients.

ADVERSE REACTIONS

Post-Marketing Adverse Reactions

The following adverse reactions have been identified during post approval use of Sodium Chloride Injection, USP. Because these reactions are reported voluntarily from a population of uncertain size, it is not always possible to reliably estimate their frequency or establish a causal relationship to drug exposure.

The following adverse reactions have been reported in the post-marketing experience during use of Sodium Chloride Injection, USP and include the following:

General disorders and administration site conditions: Infusion site erythema, injection site streaking, burning sensation, and infusion site urticaria

Hypersensitivity reactions: Hypotension, pyrexia, tremor, chills, urticaria, rash, and pruritus.

Metabolism and nutrition disorders: Hypernatremia*, hyponatremia, hyperchloremic metabolic acidosis.

Nervous System Disorders: Hyponatremic encephalopathy

* Adverse reaction of hyponatremia is only related to 0.9% Sodium Chloride Injection, USP

If an adverse reaction does occur, discontinue the infusion, evaluate the patient, institute appropriate therapeutic countermeasures and save the remainder of the fluid for examination if deemed necessary.

OVERDOSAGE

Excessive administration of:

- 0.45% Sodium Chloride Injection, USP can cause hyponatremia and hypernatremia. Both hypo- and hypernatremia can lead to CNS manifestations, including seizures, coma, cerebral edema and death.
- 0.9% Sodium Chloride Injection, USP can cause hypernatremia.
- Sodium Chloride Injection, USP can cause fluid overload (which can lead to pulmonary and/or peripheral edema). See WARNINGSand ADVERSE REACTIONS.

When assessing an overdose, any additives in the solution must also be considered. The effects of an overdose may require immediate medical attention and treatment.

Interventions include discontinuation of Sodium Chloride Injection, USP administration, dose reduction, and other measures as indicated for the specific clinical constellation (e.g., monitoring of fluid balance, electrolyte concentrations and acid base balance).

DOSAGE AND ADMINISTRATION

Important Preparation and Administration Instructions

- Sodium Chloride Injection, USP is intended for intravenous administration using sterile equipment.
- Prior to infusion, visually inspect the solution for particulate matter and discoloration. The solution should be clear, and there should be no precipitates. Do not administer unless solution is clear, and container is undamaged.
- To reduce the risk of air embolism, adhere to the following preparation instructions for Lactated Ringer’s Injection, USP:
  - Use a non-vented infusion set or close the vent on a vented set.
  - Use a dedicated line without any connections (do not connect flexible containers in series).
  - The use of pressure infusion is notrecommended as a method to increase flow rates. However, if pressure infusion is required, ensure that any air within the bag is fully evacuated prior to initiation of infusion.
  - If using a pumping device to administer Sodium Chloride Injection, turn off the pump before the container is empty.
  - Do not mix or administer 0.45% Sodium Chloride Injection, USP through the same administration set with whole blood or cellular blood components.

Dosing Information

The choice of product, dosage, volume, rate, and duration of administration is dependent upon the age, weight and clinical condition of the patient and concomitant therapy, and administration should be determined by a physician experienced in intravenous fluid therapy.

Introduction of Additives

Additives may be incompatible.

Evaluate all additions to the plastic container for compatibility and stability of the resulting preparation. Consult with a pharmacist, if available.

If, in the informed judgment of the physician, it is deemed advisable to introduce additives, use aseptic technique. Mix thoroughly when additives have been introduced. After addition, if there is a discoloration and/or the appearance of precipitates, insoluble complexes or crystals, do not use. Do not store solutions containing additives. Discard any unused portion.

HOW SUPPLIED

The available size of each injection in VIAFLEX plastic containers are shown below:

 | Size (mL) | NDC
 | 100 | 84549-049-48
 | Single pack

Exposure of pharmaceutical products to heat should be minimized. Avoid excessive heat. It is recommended the product be stored at room temperature (25°C/77°F); brief exposure up to 40°C/104°F does not adversely affect the product.

DIRECTIONS FOR USE OF VIAFLEX PLASTIC CONTAINER

For Information on Risk of Air Embolism – see DOSAGE AND ADMINISTRATION.

To Open

Tear overwrap down side at slit and remove solution container. Visually inspect the container. If the outlet port protector is damaged, detached, or not present, discard container as solution path sterility may be impaired. Some opacity of the plastic due to moisture absorption during the sterilization process may be observed. This is normal and does not affect the solution quality or safety. The opacity will diminish gradually. Check for minute leaks by squeezing inner bag firmly. If leaks are found, discard solution as sterility may be impaired. If supplemental medication is desired, follow directions below.

Preparation for Administration

1. Suspend container from eyelet support.
2. Remove protector from outlet port at bottom of container.
3. Attach administration set. Refer to complete directions accompanying set.

To Add Medication

Additives may be incompatible

To add medication before solution administration

1. Prepare medication site.
2. Using syringe with 19 to 22 gauge needle, puncture resealable medication port and inject.
3. Mix solution and medication thoroughly. For high density medication such as potassium chloride, squeeze ports while ports are upright and mix thoroughly.

To add medication during solution administration

1. Close clamp on the set.
2. Prepare medication site.
3. Using syringe with 19 to 22 gauge needle, puncture resealable medication port and inject.
4. Remove container from IV pole and/or turn to an upright position.
5. Evacuate both ports by squeezing them while container is in the upright position.
6. Mix solution and medication thoroughly.
7. Return container to in-use position and continue administration.

Baxter Healthcare Corporation
Deerfield, IL 60015 USA
Printed in USA

Baxter and Viaflex are trademarks of Baxter International Inc.